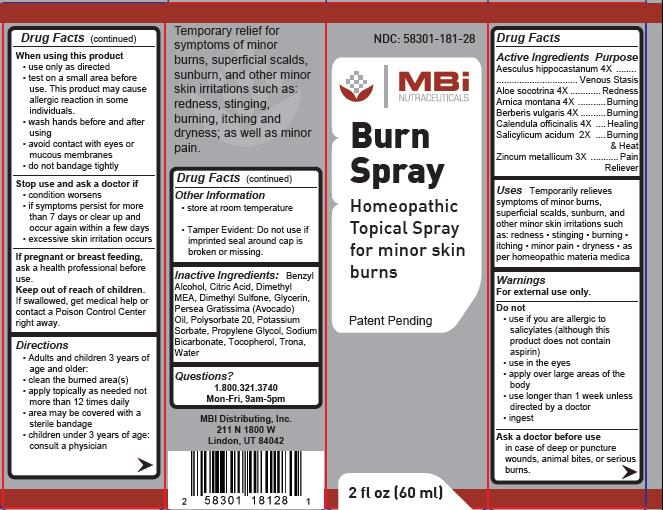 DRUG LABEL: Burn
NDC: 58301-181 | Form: SPRAY
Manufacturer: MBI Distributing Inc.
Category: homeopathic | Type: HUMAN OTC DRUG LABEL
Date: 20110728

ACTIVE INGREDIENTS: AESCULUS HIPPOCASTANUM FLOWER 4 [hp_X]/60 mL; ALOE 4 [hp_X]/60 mL; ARNICA MONTANA 4 [hp_X]/60 mL; BERBERIS VULGARIS ROOT BARK 4 [hp_X]/60 mL; CALENDULA OFFICINALIS FLOWERING TOP 4 [hp_X]/60 mL; SALICYLIC ACID 2 [hp_X]/60 mL; ZINC SULFATE HEPTAHYDRATE 3 [hp_X]/60 mL
INACTIVE INGREDIENTS: WATER; PROPYLENE GLYCOL; POLYSORBATE 20; GLYCERIN; SODIUM BICARBONATE; DIMETHYL SULFONE; CITRIC ACID MONOHYDRATE; POTASSIUM SORBATE; BENZYL ALCOHOL; AVOCADO OIL; ALPHA-TOCOPHEROL

ACTIVE INGREDIENT

Aesculus hippocastanum 4x, Aloe socotrina 4x, Arnica montana 4x, Berberis vulgaris 4x, Calendula officinalis 4x, Salicylicum acidum 2x, Zincum metallicum 3x

INACTIVE INGREDIENT

deionized water, propylene glycol, polysorbate 20, glycerine, sodium bicarbonate, MSM, Dimethylaminoethanol, citric acid, potassium sorbate, benzyl alcohol, trace minerals (trona), avocado oil, and vitamin E

INDICATIONS AND USAGE

Temporarily relieves symptoms of minor burns, superficial scalds, sunburn, and other minor skin irritations such as:

- redness
- stinging
- burning
- itching
- minor pain
- dryness
- as per homeopathic materia medica

Directions

- Adults and children 3 years of age and older:
- clean the burned area(s)
- apply topically as needed not more than 12 times daily
- area may be covered with a sterile bandage
- children under 3 years of age: consult a physician

PURPOSE

Aesculus hippocastanum...................................................Venous Stasis

Aloe socotrina...........................................................................Redness

Arnica montana...........................................................................Burning

Berberis vulgaris..........................................................................Burning

Calendula officinalis.....................................................................Healing

Salicylicum acidum.......................................................Burning and Heat

Zincum metallicum.............................................................Pain Reliever

KEEP OUT OF REACH OF CHILDREN

Keep out of the reach of children. If swallowed, get medical help or contact a Poison Control Center right away.

WARNINGS

For external use only.

Questions?
1.800.321.3740
Mon-Fri, 9am-5pm

Do not

- use if you are allergic to salicylates (although this product does not contain aspirin)
- use in the eyes
- apply over large areas of the body
- use longer than 1 week unless directed by a doctor
- ingest

Ask a doctor before use in case of deep or puncture wounds, animal bites, or serious burns.

When using this product

- use only as directed
- test on a small area before use. This product may cause allergic reaction in some individuals.
- wash hands before and after using
- avoid contact with eyes or mucous membranes
- do not bandage tightly

Stop use and ask a doctor if

- condition worsens
- if symptoms persist for more than 7 days or clear up and occur again within a few days
- excessive skin irritation occurs

STORAGE AND HANDLING

- store at room temperature
- Tamper Evident: Do not use if imprinted seal around cap is broken or missing.